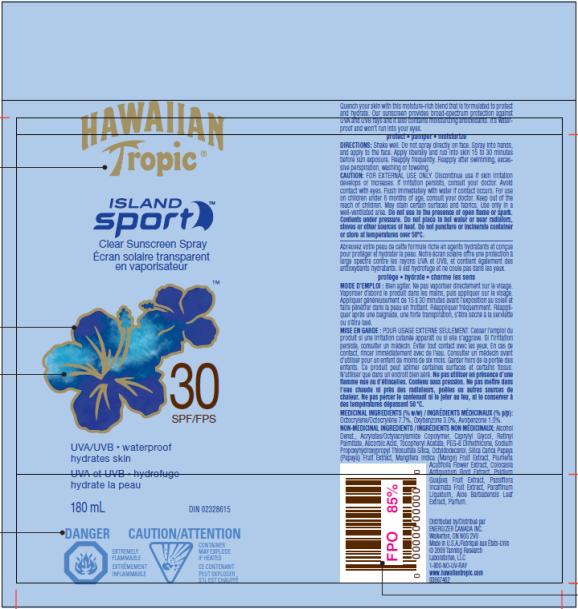 DRUG LABEL: Hawaiian Tropic Island Sport SPF 30 for Canada
NDC: 17630-2038 | Form: SPRAY
Manufacturer: Accra-Pac, Inc.
Category: otc | Type: HUMAN OTC DRUG LABEL
Date: 20100328

ACTIVE INGREDIENTS: OCTOCRYLENE 0.077 mL/1 mL; OXYBENZONE 0.03 mL/1 mL; AVOBENZONE 0.01 mL/1 mL
INACTIVE INGREDIENTS: CAPRYLYL GLYCOL; VITAMIN A PALMITATE; ASCORBIC ACID; .ALPHA.-TOCOPHEROL ACETATE, D-; OCTYLDODECANOL; SILICON DIOXIDE; PAPAYA; MANGO; PLUMERIA EXTRACT; GUAVA; PASSIFLORA INCARNATA TOP; MINERAL OIL; ALOE VERA LEAF

Hawaiian Tropic Island Sport SPF 30 for Canada

Active Ingredients

Octocrylene 0.077mL / 1mL

Oxybenzone 0.03mL / 1mL

Avobenzone 0.01mL / 1mL

DIRECTIONS:

Shake well. Do not spray directly on face. Spray into hands, and apply to the face. Apply liberally and rub into skin 15 to 30 minutes before sun exposure. Reapply frequently. Reapply after swimming, excessive perspiration, washing or toweling.

CAUTION:

FOR EXTERNAL USE ONLY. Discontinue use if skin irritation develops or increases. If irritation persists, consult your doctor. Avoid contact with eyes. Flush immediately with water if contact occurs. For use on children under 6 months of age, consult your doctor. Keep out of the reach of children. May stain certain surfaces and fabrics. Use only in a well-ventilated area. Do not use in the presence of open flame or spark. Contents under pressure. Do not place in hot water or near radiators, stoves or other sources of heat. Do not puncture or incinerate container or store at temperatures over 50ºC.

MODE D’EMPLOI :

Bien agiter. Ne pas vaporiser directement sur le visage. Vaporiser d’abord le produit dans les mains, puis appliquer sur le visage. Appliquer généreusement de 15 à 30 minutes avant l’exposition au soleil et faire pénétrer dans la peau en frottant. Réappliquer fréquemment. Réappliquer après une baignade, une forte transpiration, s’être séché à la serviette ou s’être lavé.

MISE EN GARDE :

POUR USAGE EXTERNE SEULEMENT. Cesser l’emploi du produit si une irritation cutanée apparaît ou si elle s’aggrave. Si l’irritation persiste, consulter un médecin. Éviter tout contact avec les yeux. En cas de contact, rincer immédiatement avec de l’eau. Consulter un médecin avant d’utiliser pour un enfant de moins de six mois. Garder hors de la portée des enfants. Ce produit peut abîmer certaines surfaces et certains tissus. N’utiliser que dans un endroit bien aéré. Ne pas utiliser en présence d’une flamme nue ou d’étincelles. Contenu sous pression. Ne pas mettre dans l’eau chaude ni près des radiateurs, poêles ou autres sources de chaleur. Ne pas percer le contenant ni le jeter au feu, ni le conserver à des températures dépassant 50 ºC.

NON-MEDICINAL INGREDIENTS/INGRÉDIENTS NON MÉDICINAUX:

Alcohol Denat., Acrylates/Octylacrylamide Copolymer, Caprylyl Glycol, Retinyl Palmitate, Ascorbic Acid, Tocopheryl Acetate, PEG-8 Dimethicone, Sodium Propoxyhydroxypropyl Thiosulfate Silica, Octyldodecanol, Silica, Carica Papaya (Papaya) Fruit Extract, Mangifera Indica (Mango) Fruit Extract, Plumeria Acutifolia Flower Extract, Colocasia Antiquorum Root Extract, Psidium Guajava Fruit Extract, Passiflora Incarnata Fruit Extract, Paraffinum Liquidum, Aloe Barbadensis Leaf Extract, Parfum.

Distributed by/Distribué par
ENERGIZER CANADA INC.
Walkerton, ON N0G 2V0
Made in U.S.A./Fabriqué aux États-Unis
© 2009 Tanning Research
Laboratories, LLC
1-800-NO-UV-RAY
www.hawaiiantropic.com

PRINCIPAL DISPLAY PANEL

HAWAIIAN
Tropic®
ISLAND
sport TM
Clear Sunscreen Spray
Écran solaire transparent
en vaporisateur
30 SPF/FPS
UVA/UVB waterproof
hydrates skin
UVA et UVB hydrofuge
hydrate la peau
180 mL